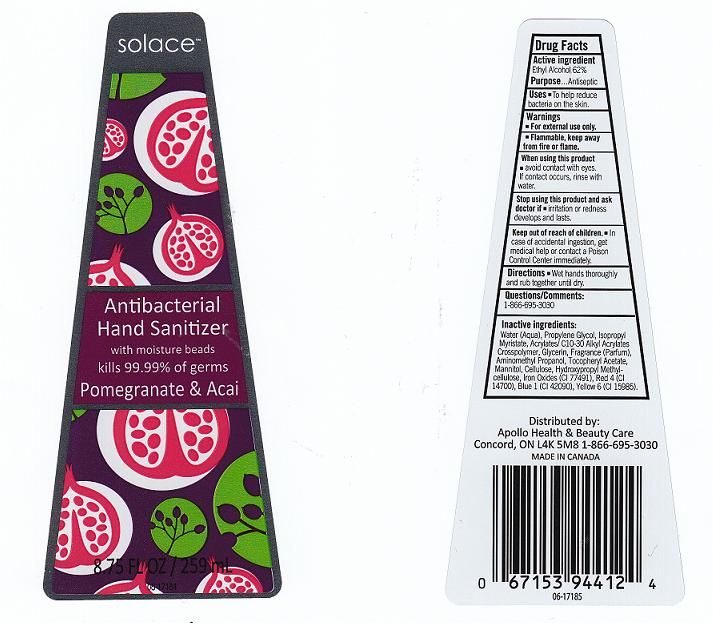 DRUG LABEL: ANTIBACTERIAL HAND SANITIZER
NDC: 63148-271 | Form: GEL
Manufacturer: APOLLO HEALTH AND BEAUTY CARE
Category: otc | Type: HUMAN OTC DRUG LABEL
Date: 20110412

ACTIVE INGREDIENTS: ALCOHOL 62 mL/100 mL
INACTIVE INGREDIENTS: WATER; PROPYLENE GLYCOL; ISOPROPYL MYRISTATE; CARBOMER COPOLYMER TYPE A; GLYCERIN; AMINOMETHYLPROPANOL; .ALPHA.-TOCOPHEROL ACETATE, D-; MANNITOL; POWDERED CELLULOSE; HYPROMELLOSES; FERRIC OXIDE RED; FD&C RED NO. 4; FD&C BLUE NO. 1; FD&C YELLOW NO. 6

DRUG FACTS

ACTIVE INGREDIENT

ETHYL ALCOHOL 62 PERCENT

PURPOSE

ANTISEPTIC

USES

TO HELP REDUCE BACTERIA ON THE SKIN.

WARNINGS

FOR EXTERNAL USE ONLY.

FLAMMABLE. KEEP AWAY FROM FIRE OR FLAME.

WHEN USING THIS PRODUCT

AVOID CONTACT WITH EYES. IF CONTACT OCCURS, RINSE WITH WATER.

STOP USING THIS PRODUCT AND ASK DOCTOR IF

IRRITATION OR REDNESS DEVELOPS OR LASTS.

KEEP OUT OF REACH OF CHILDREN

IN CASE OF ACCIDENTAL INGESTION, GET MEDICAL HELP OR CONTACT A POISON CONTROL CENTER IMMEDIATELY.

DIRECTIONS

WET HANDS THOROUGHLY AND RUB TOGETHER UNTIL DRY.

QUESTIONS OR COMMENTS

1-866-695-3030

INACTIVE INGREDIENTS

WATER, PROPYLENE GLYCOL, ISOPROPYL MYRISTATE, ACRYLATES/C10-30 ALKYL ACRYLATES CROSSPOLYMER, GLYCERIN, FRAGRANCE, AMINOMETHYL PROPANOL, TOCOPHERYL ACETATE, MANNITOL, CELLULOSE, HYDROXYPROPYL METHYLCELLULOSE, IRON OXIDES (CI 77491), RED 4 (CI 14700), BLUE 1 (CI 42090), YELLOW 6 (CI 15985).